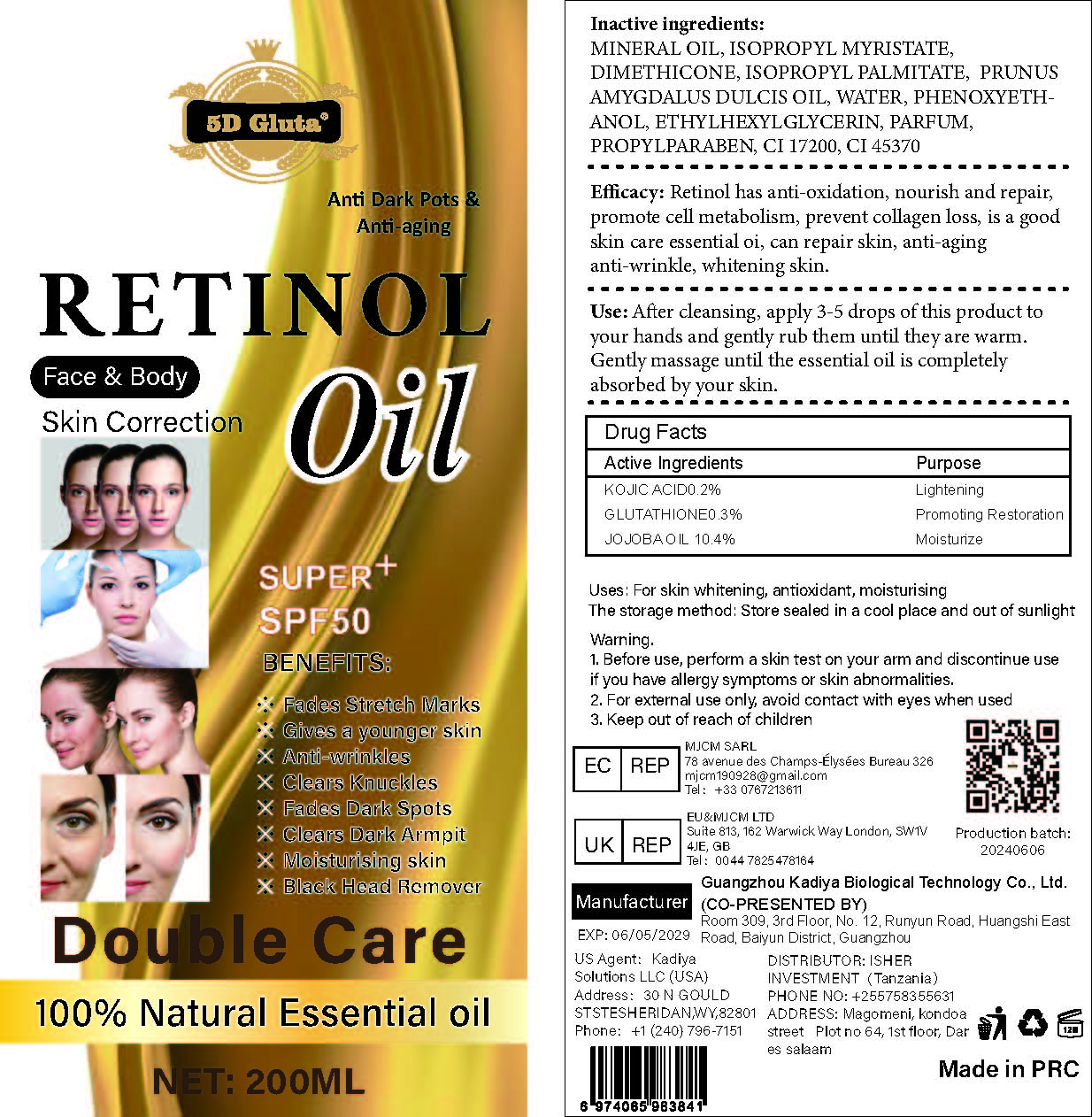 DRUG LABEL: RetinolOil
NDC: 84423-059 | Form: OIL
Manufacturer: Guangzhou Kadiya Biotechnology Co., Ltd.
Category: otc | Type: HUMAN OTC DRUG LABEL
Date: 20241217

ACTIVE INGREDIENTS: SIMMONDSIA CHINENSIS (JOJOBA) SEED OIL 20.8 g/200 mL; GLUTATHIONE 0.6 g/200 mL; KOJIC ACID 0.4 g/200 mL
INACTIVE INGREDIENTS: WATER; ISOPROPYL MYRISTATE; CI 17200; MINERAL OIL; DIMETHICONE 1000; PHENOXYETHANOL; PROPYLPARABEN; ISOPROPYL PALMITATE; CI 45370; ETHYLHEXYLGLYCERIN; SQUALANE; LAVANDULA ANGUSTIFOLIA (LAVENDER) OIL; PRUNUS AMYGDALUS DULCIS (SWEET ALMOND) OIL

PURPOSE

For skin whitening, antioxidant, moisturising

INACTIVE INGREDIENT

MINERAL OIL，ISOPROPYL MYRISTATE，DIMETHICONE，ISOPROPYL PALMITATE， PRUNUS AMYGDALUS DULCIS OIL，WATER，PHENOXYETHANOL，ETHYLHEXYLGLYCERIN，PARFUM，PROPYLPARABEN，CI 17200，CI 45370

WARNINGS

1、Before use, perform a skin test on your arm and discontinue use if you have allergy symptoms or skin abnormalities.
2、For external use only, avoid contact with eyes when used
3、Keep out of reach of children

INDICATIONS AND USAGE

Retinol has anti-oxidation, nourish and repair, promote cell metabolism, prevent collagen loss, is a good skin care essential oi, can repair skin, anti-aging anti-wrinkle, whitening skin

DOSAGE AND ADMINISTRATION

After cleansing, apply 3-5 drops of this product to your hands and gently rub them until they are warm. Gently massage until the essential oil is completely absorbed by your skin.

KEEP OUT OF REACH OF CHILDREN SECTION

Active Ingredients Purpose
KOJIC ACID0.2% Lightening
GLUTATHIONE0.3% Promoting Restoration
JOJOBA OIL 10.4% Moisturize

PACKAGE LABEL

Active Ingredients Purpose
KOJIC ACID0.2% Lightening
GLUTATHIONE0.3% Promoting Restoration
JOJOBA OIL 10.4% Moisturize

Uses：
For skin whitening, antioxidant, moisturising
The storage method：
Store sealed in a cool place and out of sunlight

Warning.
1.Before use, perform a skin test on your arm and discontinue use if you have allergy symptoms or skin abnormalities.
2、For external use only, avoid contact with eyes when used
3、Keep out of reach of children

Inactive ingredients：
MINERAL OIL，ISOPROPYL MYRISTATE，DIMETHICONE，ISOPROPYL PALMITATE， PRUNUS AMYGDALUS DULCIS OIL，WATER，PHENOXYETHANOL，ETHYLHEXYLGLYCERIN，PARFUM，PROPYLPARABEN，CI 17200，CI 45370